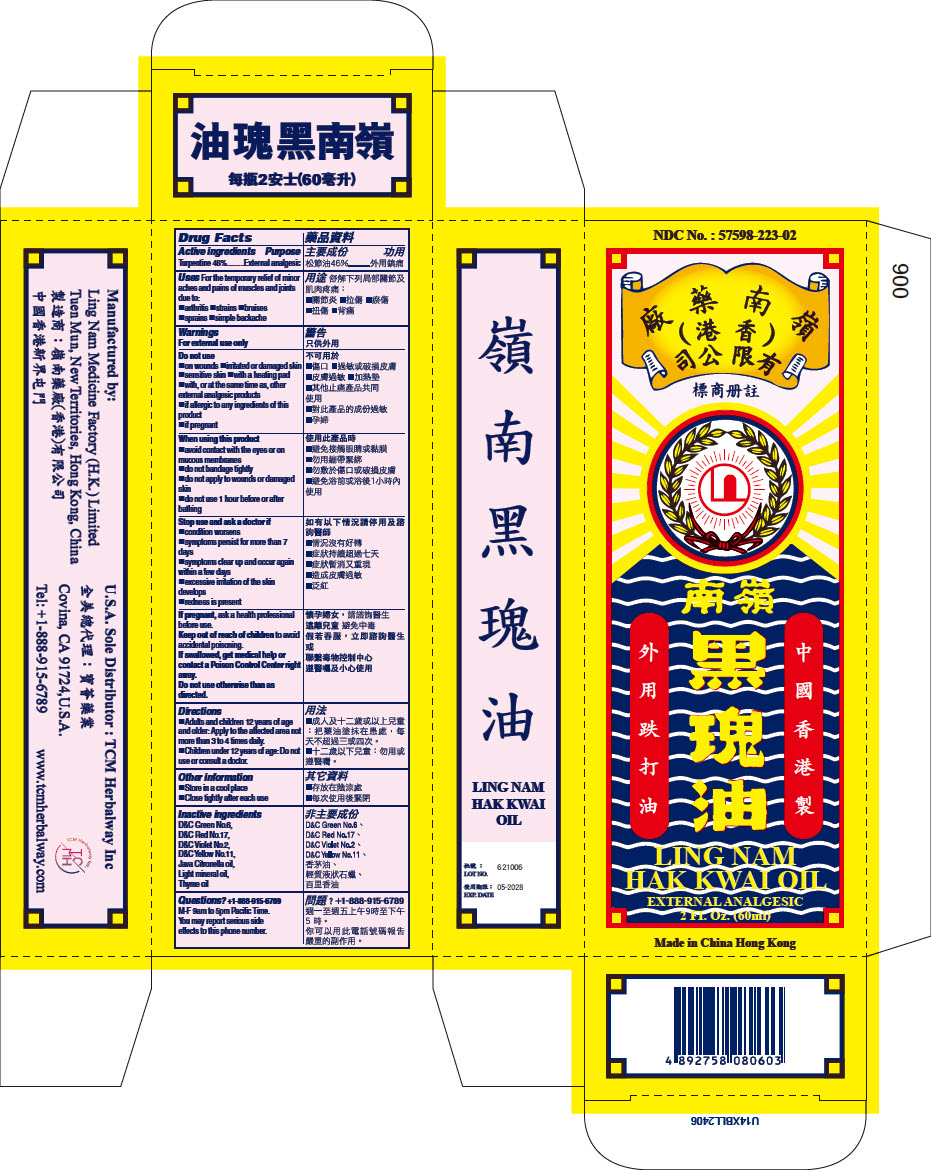 DRUG LABEL: Ling Nam Hak Kwai Oil
NDC: 57598-223 | Form: OIL
Manufacturer: Ling Nam Medicine Factory (H.K.) Ltd.
Category: otc | Type: HUMAN OTC DRUG LABEL
Date: 20240719

ACTIVE INGREDIENTS: TURPENTINE 46 g/100 mL
INACTIVE INGREDIENTS: JAVA CITRONELLA OIL; LIGHT MINERAL OIL; THYME OIL; D&C RED NO. 17; D&C YELLOW NO. 11; D&C VIOLET NO. 2; D&C GREEN NO. 6

Ling Nam Hak Kwai Oil

Drug Facts

ACTIVE INGREDIENT

Active Ingredients | Purpose
Turpentine 46% | External analgesic

Uses

For temporary relief of minor aches and pains of muscles and joints due to:

- arthritis
- strains
- bruises
- sprains
- simple backache

Warnings

For external use only

Do not use

- on wounds
- irritated or damaged skin
- sensitive skin
- with a heating pad
- with, or at the same time as, other external analgesic products
- if allergic to any ingredients of this product
- if pregnant

When using this product

- avoid contact with the eyes or on mucous membranes
- do not bandage tightly
- do not apply to wounds or damaged skin
- do not use 1 hour before or after bathing

Stop use and ask a doctor if

- condition worsens
- symptoms persist for more than 7 days
- symptoms clear up and occur again within a few days
- excessive irritation of the skin develops
- redness is present

PREGNANCY OR BREAST FEEDING

If pregnant, ask health professional before use.

Keep out of reach of children to avoid accidental poisoning.

If swallowed, get medical help or contact Poison Control Center right away.

Do not use otherwise than as directed.

Directions

- Adults and children 12 years of age and older: Apply to affected area not more than 3 to 4 times daily.
- Children under 12 years of age: Do not use or consult a doctor.

Other information

- Store in a cool place
- Close tightly after each use

Inactive ingredients

D&C Green No.6, D&C Red No.17, D&C Violet No.2, D&C Yellow No.11, Java Citronella Oil, Light mineral oil, Thyme oil

Questions?

+1-888-915-6789

M-F 9am to 5pm Pacific Time.

You may report serious side effects to this phone number.

Manufactured by:
Ling Nam Medicine Factory (H.K.) Limited
Tuen Mun, New Territories, Hong Kong, China

PRINCIPAL DISPLAY PANEL - 60 ml Bottle Box

NDC No. : 57598-223-02

LING NAM
HAK KWAI OIL

EXTERNAL ANALGESIC

2 Fl. Oz. (60ml)

Made in China Hong Kong